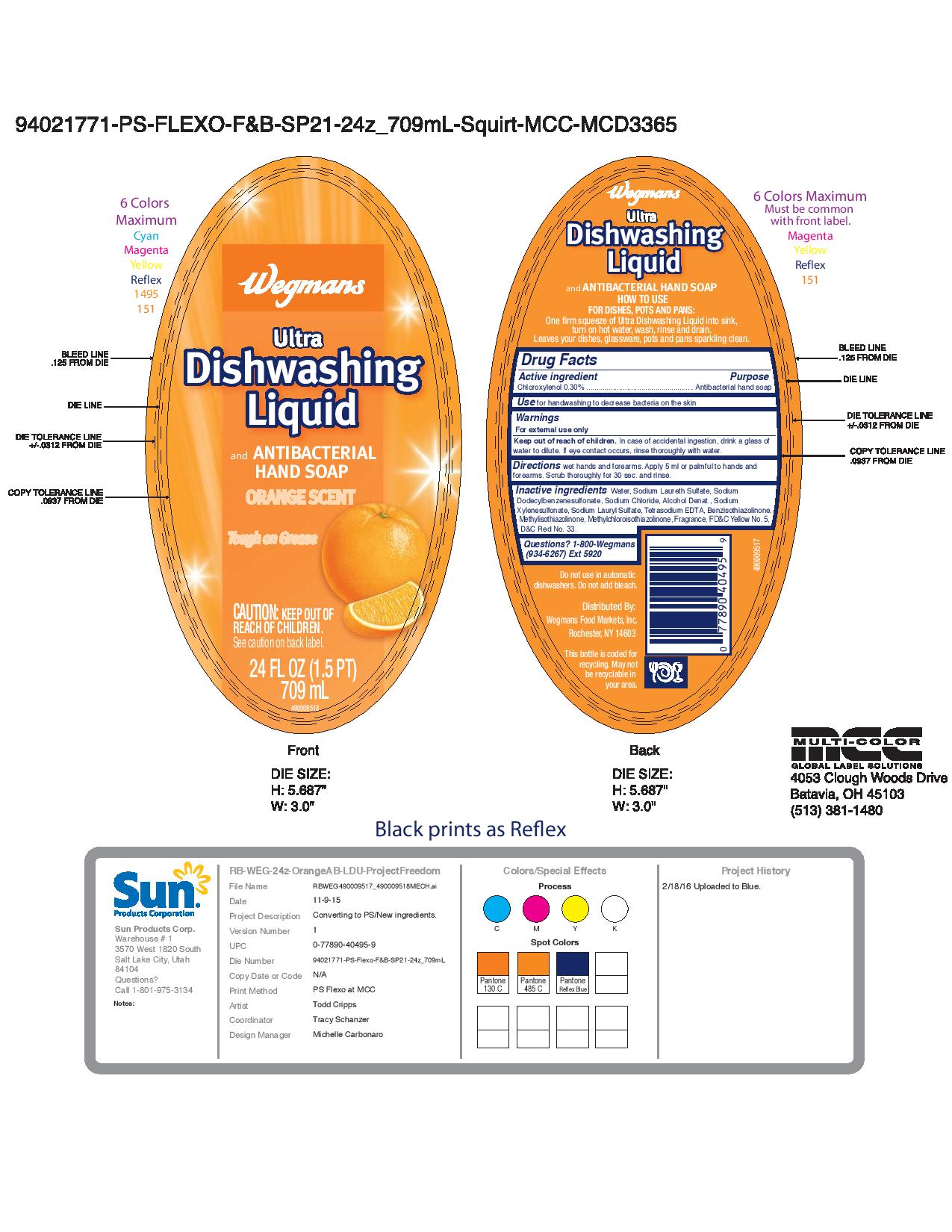 DRUG LABEL: Wegmans Ultra Dishwashing Liquid Orange Scent
NDC: 63691-035 | Form: SOAP
Manufacturer: Sun Products Corporation
Category: otc | Type: HUMAN OTC DRUG LABEL
Date: 20170313

ACTIVE INGREDIENTS: CHLOROXYLENOL 0.3 g/100 mL
INACTIVE INGREDIENTS: SODIUM LAURETH SULFATE; METHYLISOTHIAZOLINONE; FD&C YELLOW NO. 5; SODIUM CHLORIDE; WATER; ALCOHOL; SODIUM LAURYL SULFATE; SODIUM XYLENESULFONATE; METHYLCHLOROISOTHIAZOLINONE; SODIUM DODECYLBENZENESULFONATE; D&C RED NO. 33; EDETATE SODIUM; BENZISOTHIAZOLINONE

Active ingredient

Chloroxylenol 0.30%

INDICATIONS AND USAGE

Use for handwashing to decrease bacteria on the skin

WARNINGS

For external use only

Keep out of reach of children. In case of accidental ingestion, drink a glass of water to dilute. If eye contact occurs, rinse thoroughly with water.

DOSAGE AND ADMINISTRATION

Directions wet hands and forearms. Apply 5 mL or palmful to hands and forearms. Scrub thoroughly for 30 sec. and rinse.

PURPOSE

Antibacterial hand soap

INACTIVE INGREDIENT

Inactive ingredients Water, Sodium Laureth Sulfate, Sodium Dodecylbenzenesulfonate, Sodium Chloride, Alcohol Denat., Sodium Xylenesulfonate, Sodium Lauryl Sulfate, Tetrasodium EDTA, Benzisothiazolinone, Methylisothiazolinone, Methylchloroisothiazolinone, Fragrance, FD&C Yellow No. 5, D&C Red No. 33

Questions? 1-800-Wegmans (934-6267) Ext 5920